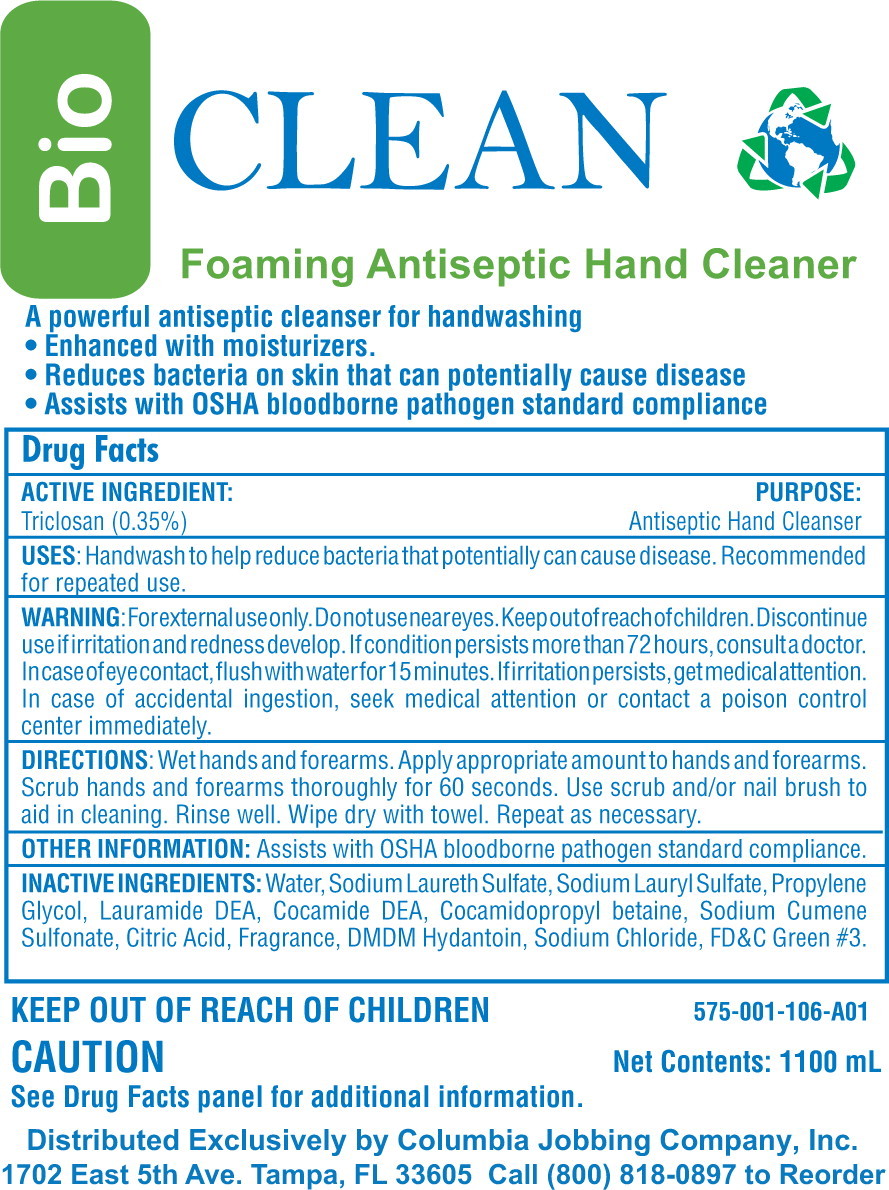 DRUG LABEL: TRICLOSAN
NDC: 53119-575 | Form: LIQUID
Manufacturer: Columbia Jobbing
Category: otc | Type: HUMAN OTC DRUG LABEL
Date: 20120912

ACTIVE INGREDIENTS: TRICLOSAN 3.15 g/1000 mL
INACTIVE INGREDIENTS: water; sodium laureth sulfate; sodium lauryl sulfate; propylene glycol; lauric diethanolamide; cocamidopropyl betaine; coco diethanolamide; citric acid monohydrate; dmdm hydantoin; sodium chloride; FD&C Green NO. 3

Drug Facts

Active Ingredient:

Triclosan (0.35%)

Purpose:

Antiseptic Hand Cleanser

Uses

- Handwash to help reduce bacteria that potentially can cause disease.
- Recommended for repeated use.

Warning

- For external use only
- Do not use near eyes

- Keep out of reach of children.

Discontinue use if irritation and redness develop. If condition persists more than 72 hours, consult a doctor.

In case of eye contact, flush with water for 15 minutes. If irritation persists, get medical attention. In case of accidental ingestion, seek medical attention or contact a poison control center immediately.

Directions

- Wet hands and forearms
- Apply appropriate amount to hands and forearms
- Scrub hands and forearms thoroughly for 60 seconds
- Use scrub and/or nail brush to aid in cleaning.
- Rinse well
- Wipe dry with towel, repeat as necessary.

Other Information

- Assists with OSHA bloodborne pathogen standard compliance

Inactive Ingredients

Water, Sodium Laureth Sulfate, Sodium Lauryl Sulfate, Propylene Glycol, Lauramide DEA, Cocamide DEA, Cocamidopropyl betaine, Sodium Cumene Sulfonate, Citric Acid, Fragrance, DMDM Hydantoin, Sodium Chloride, FD&C Green #3.

PACKAGE LABEL

Principal Display Panel

Bio CLEAN

Foaming Antiseptic Hand Cleaner

A powerful antiseptic cleanser for handwashing

- Enhanced with moisturizers
- Reduces bacteria on skin that can potentially cause disease
- Assists with OSHA bloodborne pathogen standard compliance

KEEP OUT OF REACH OF CHILDREN

CAUTION

See Drug Facts for panel for additional information.